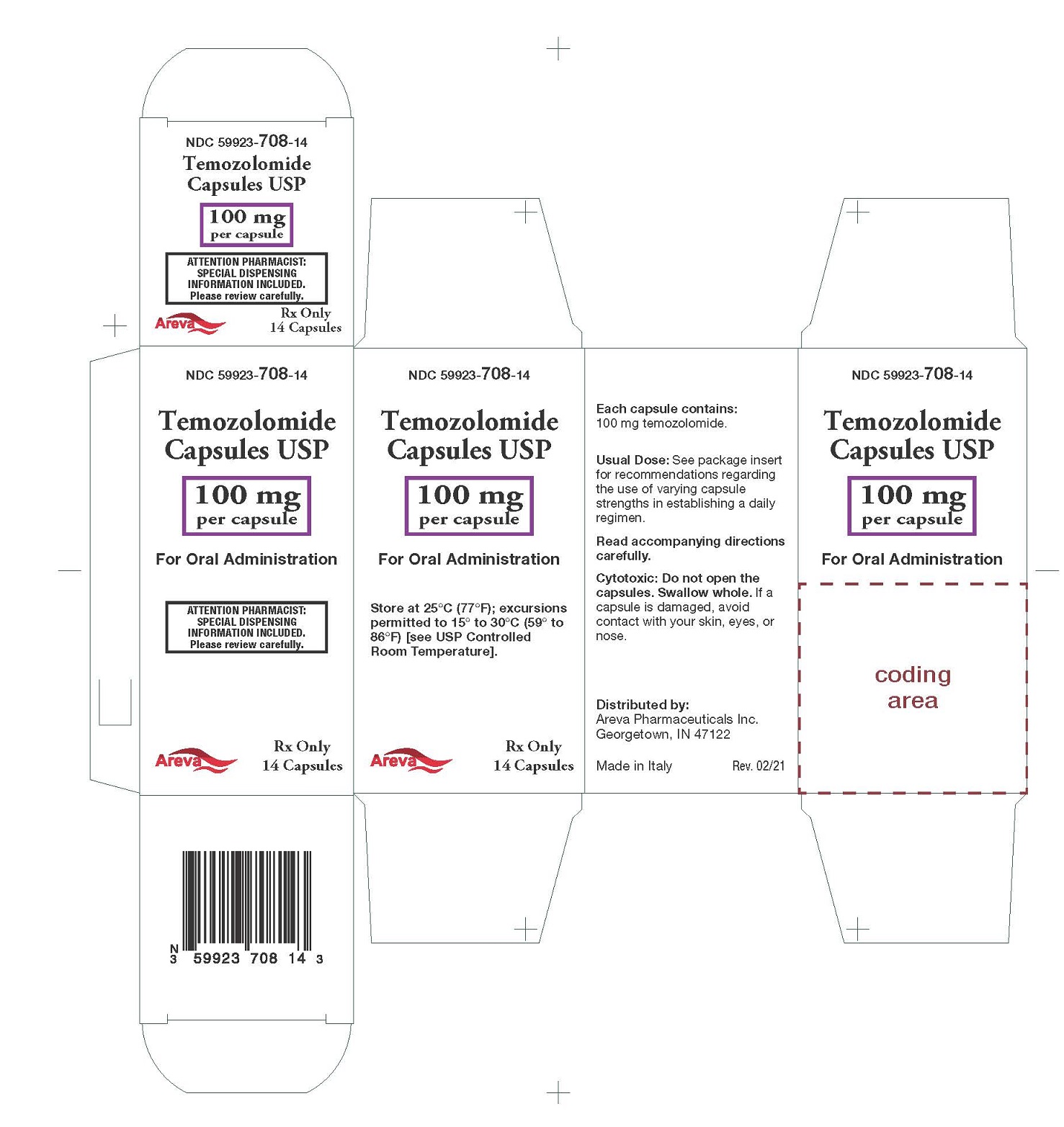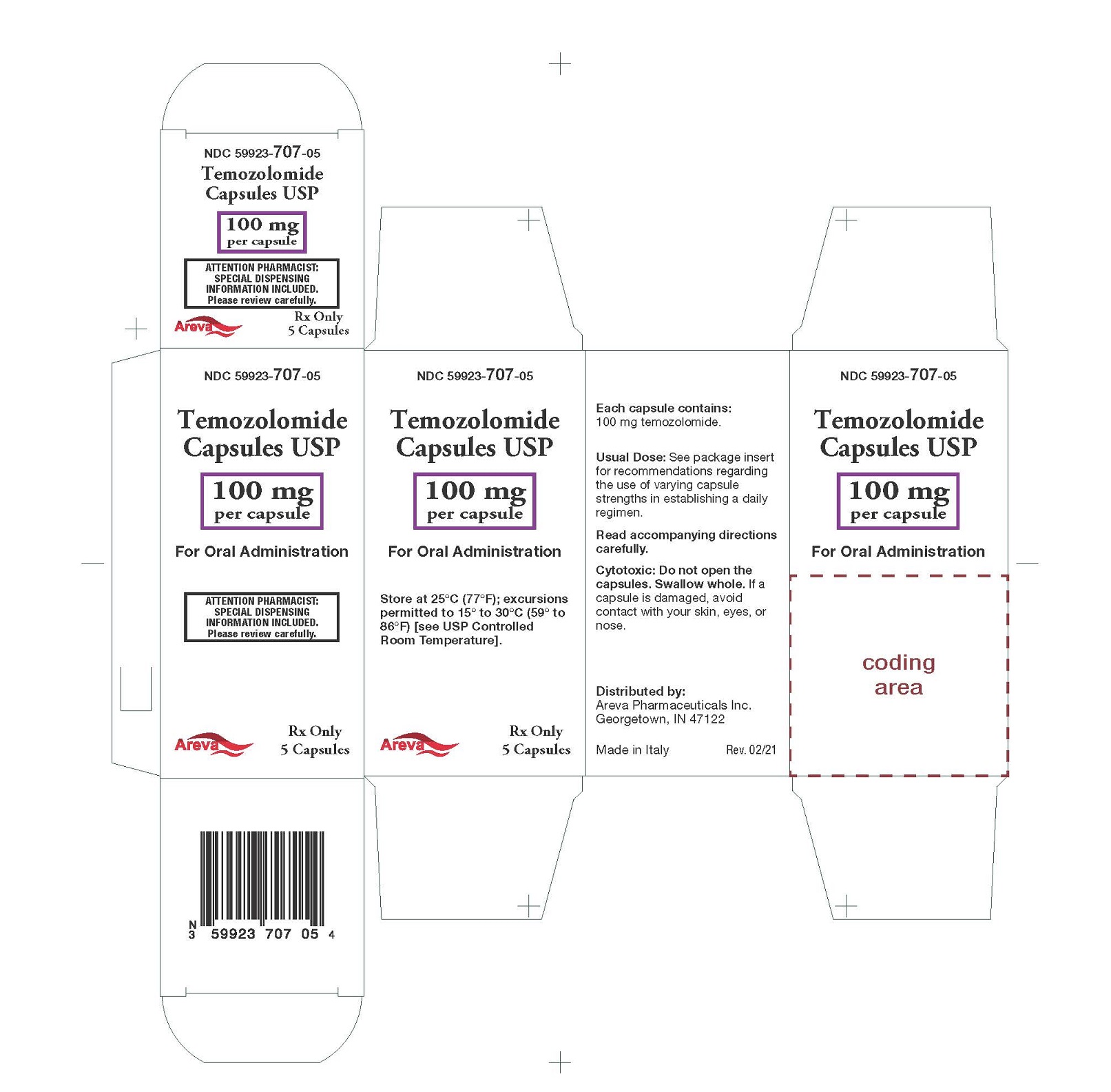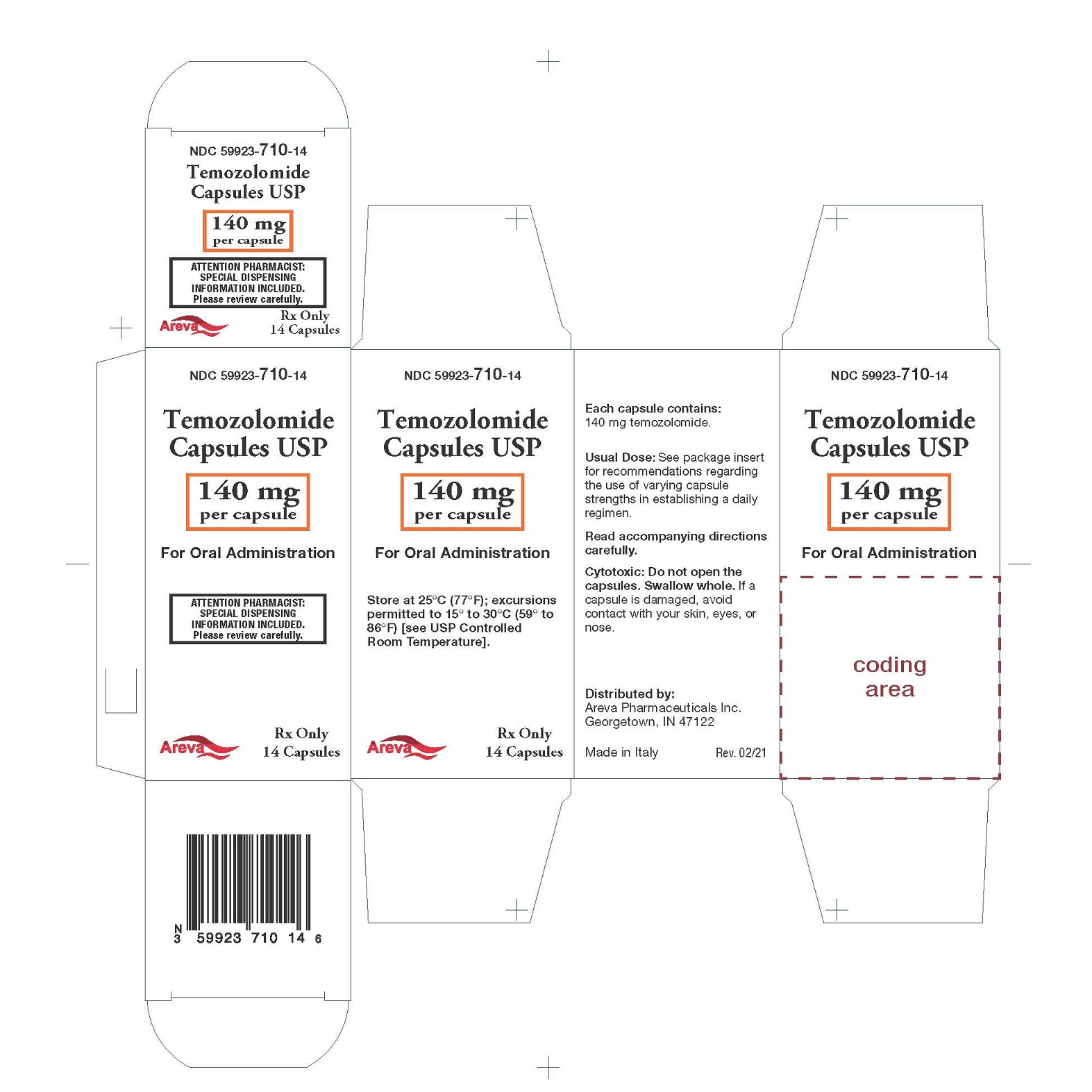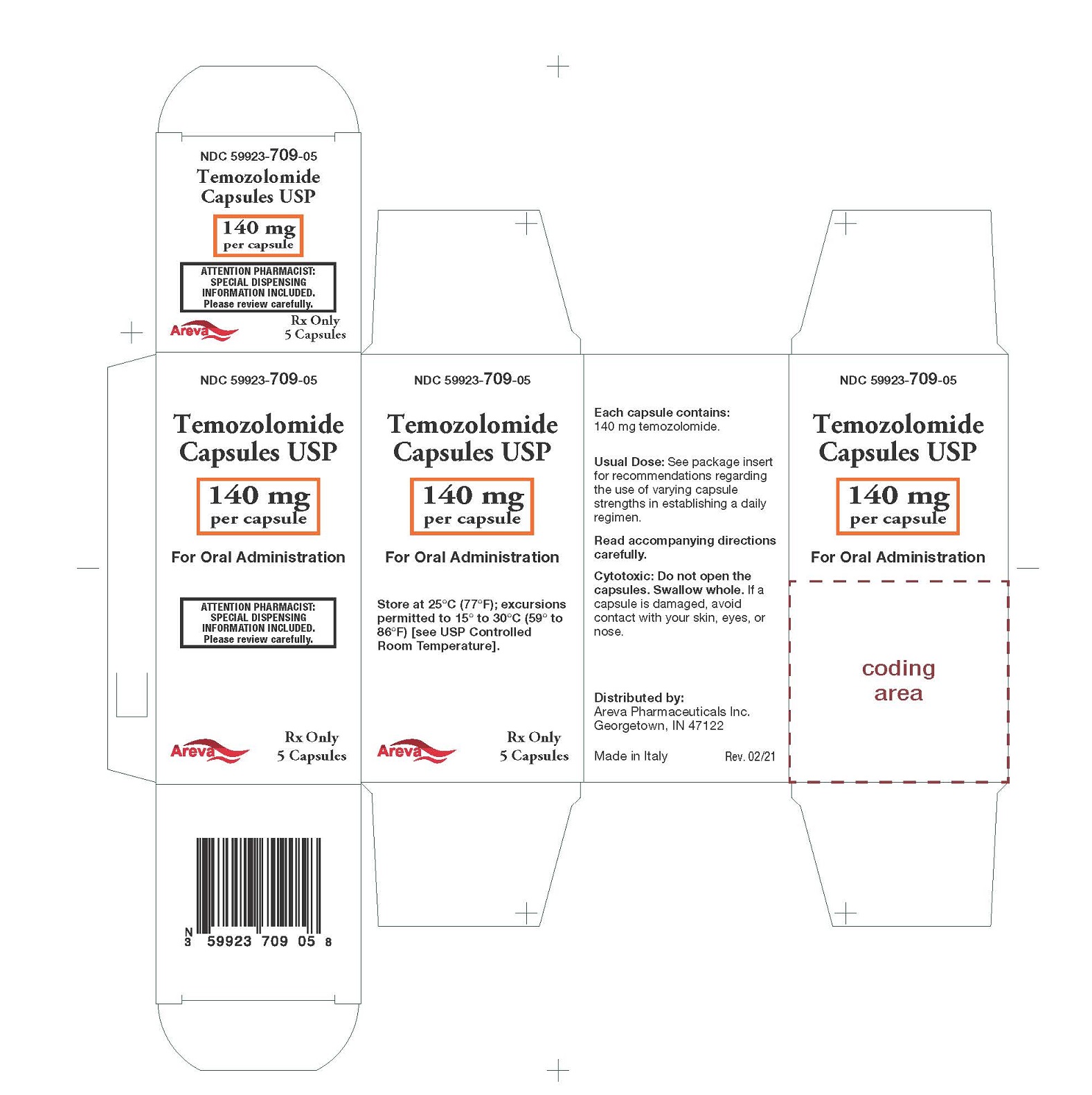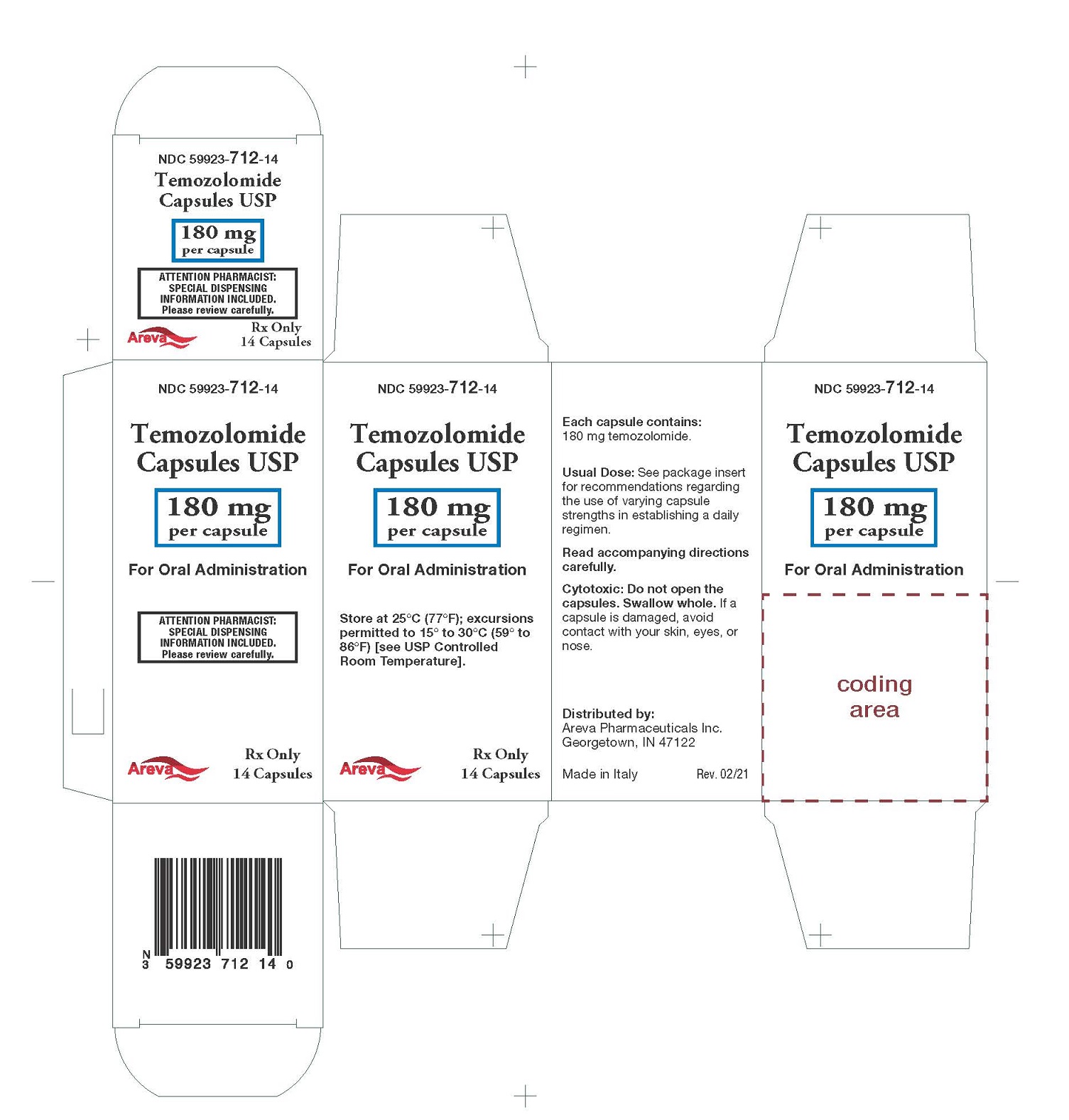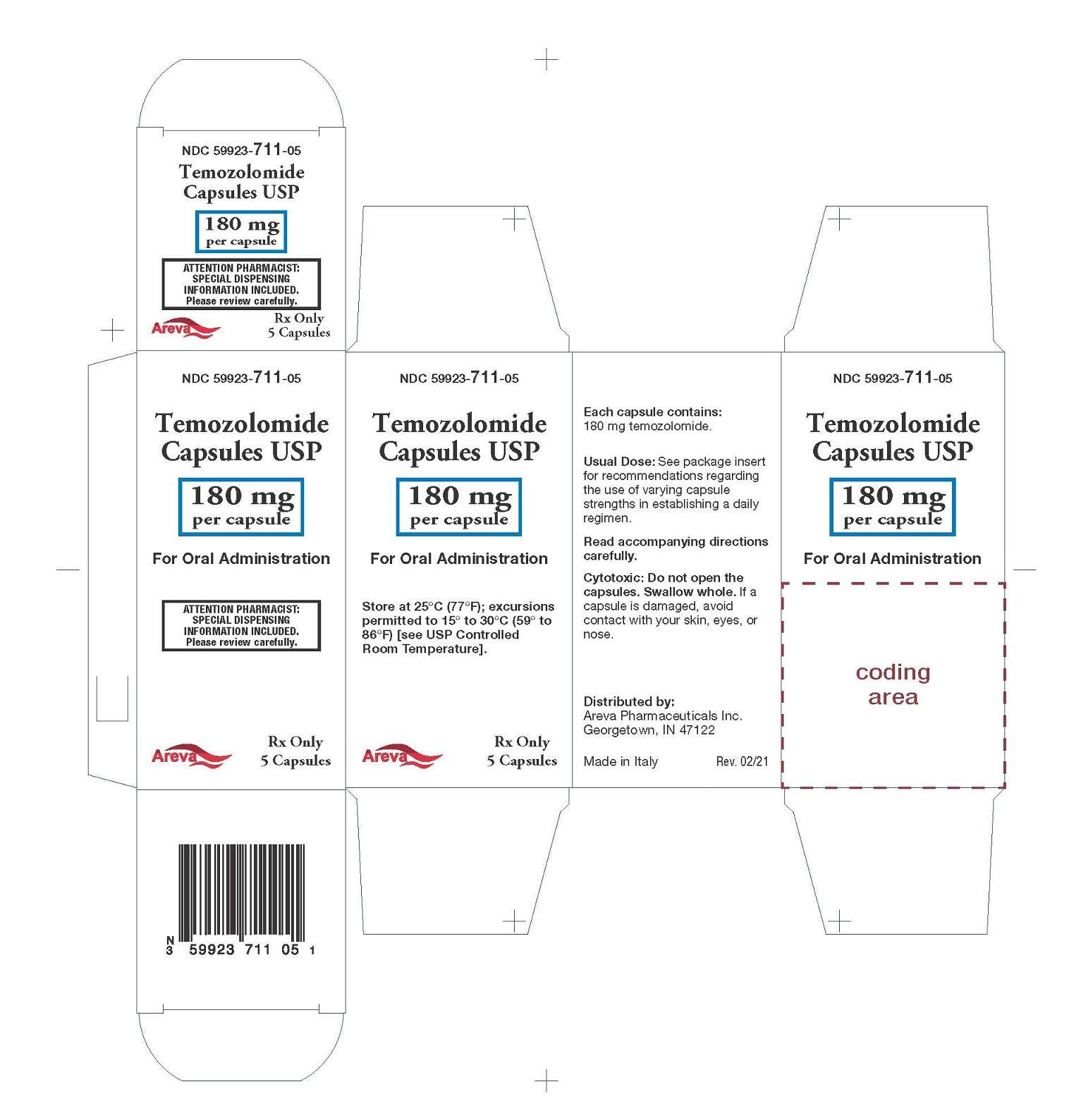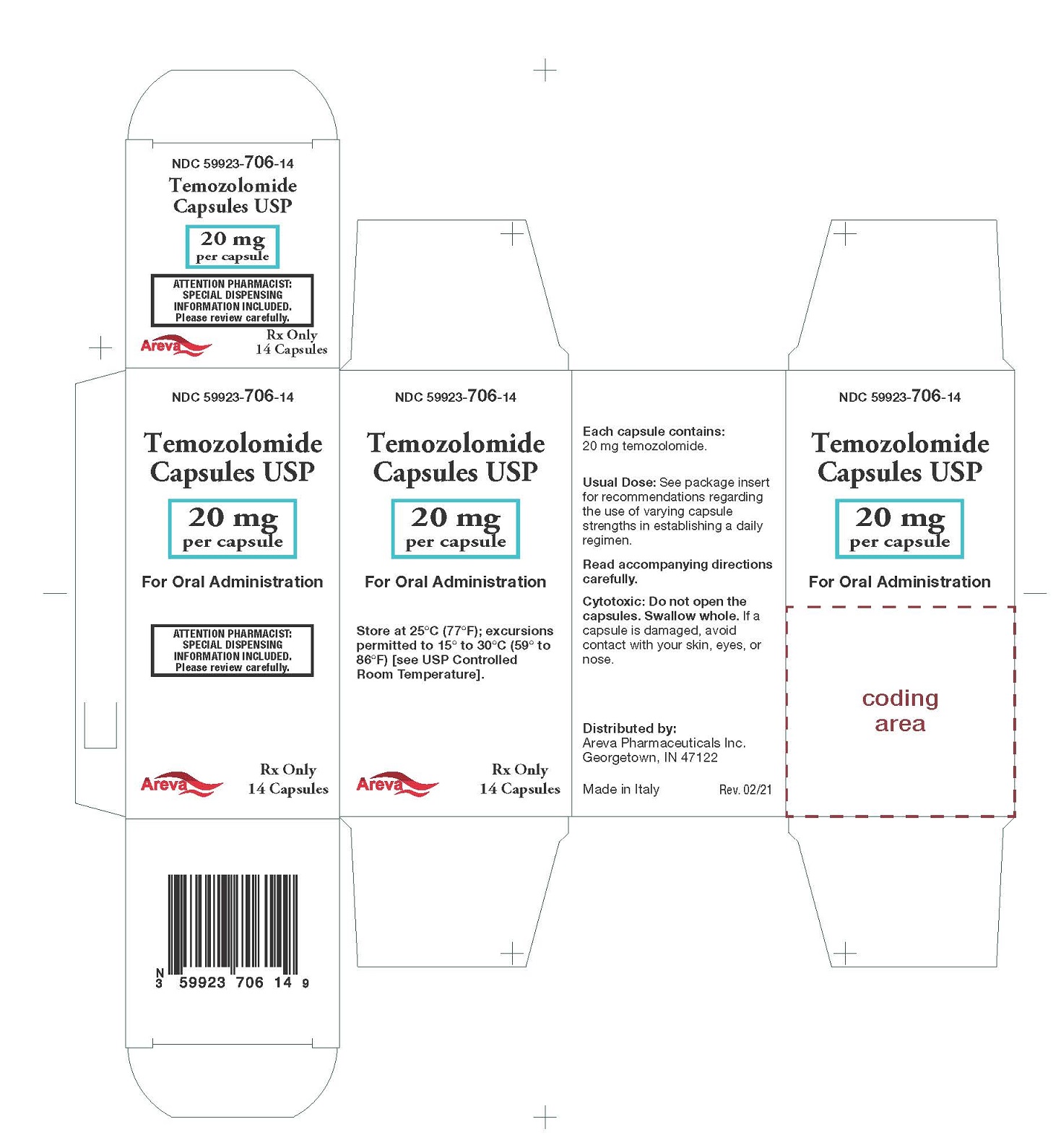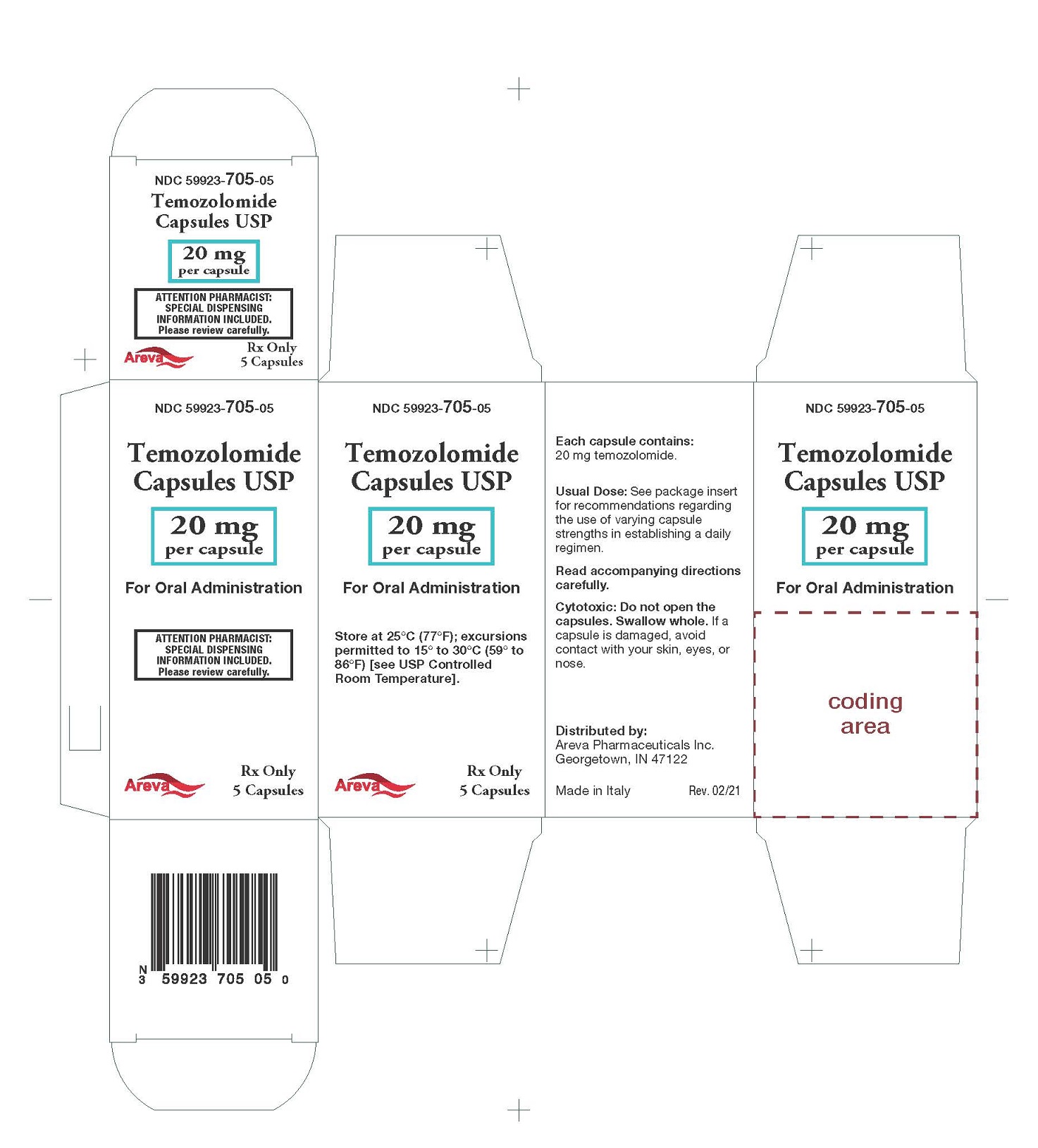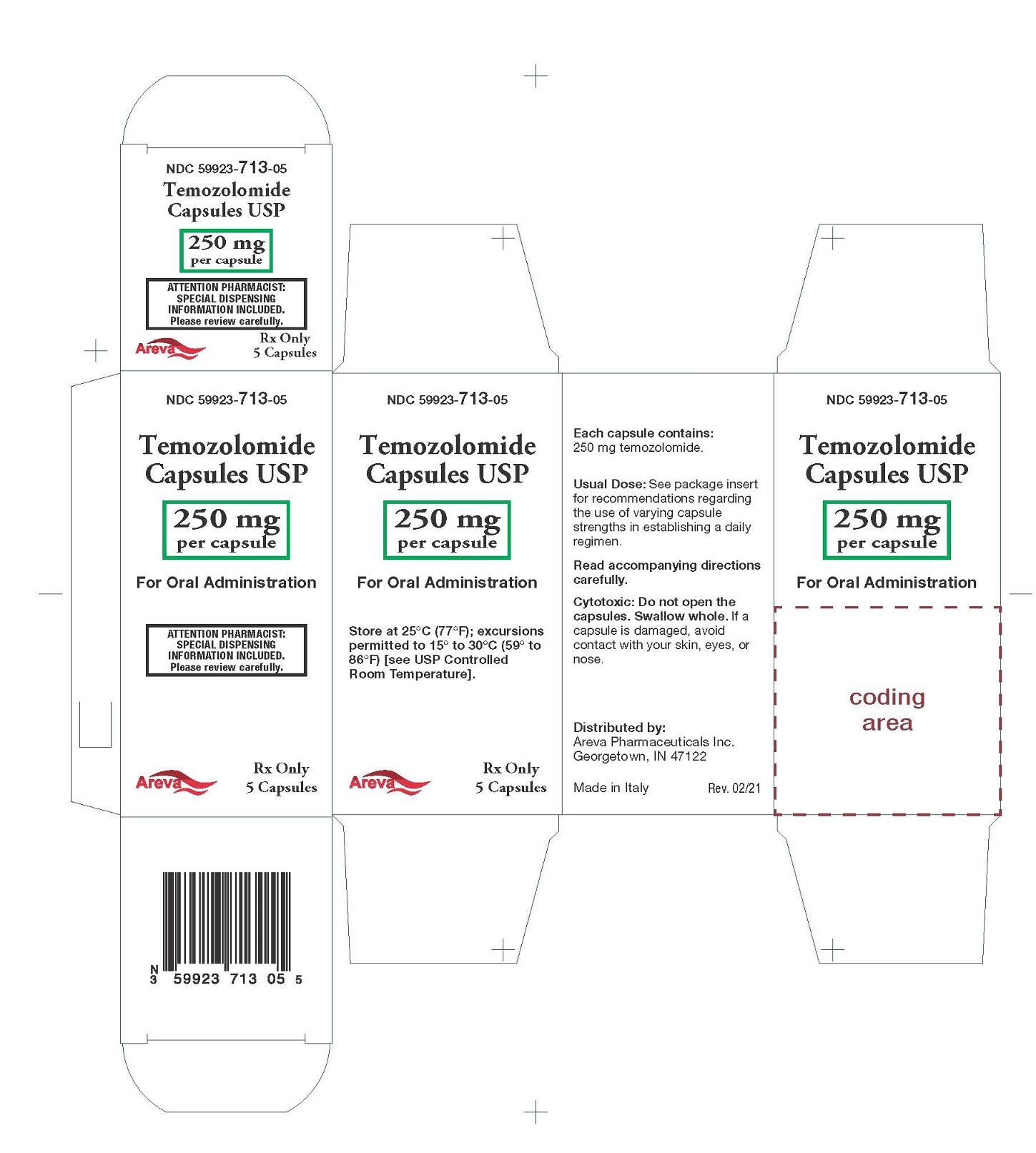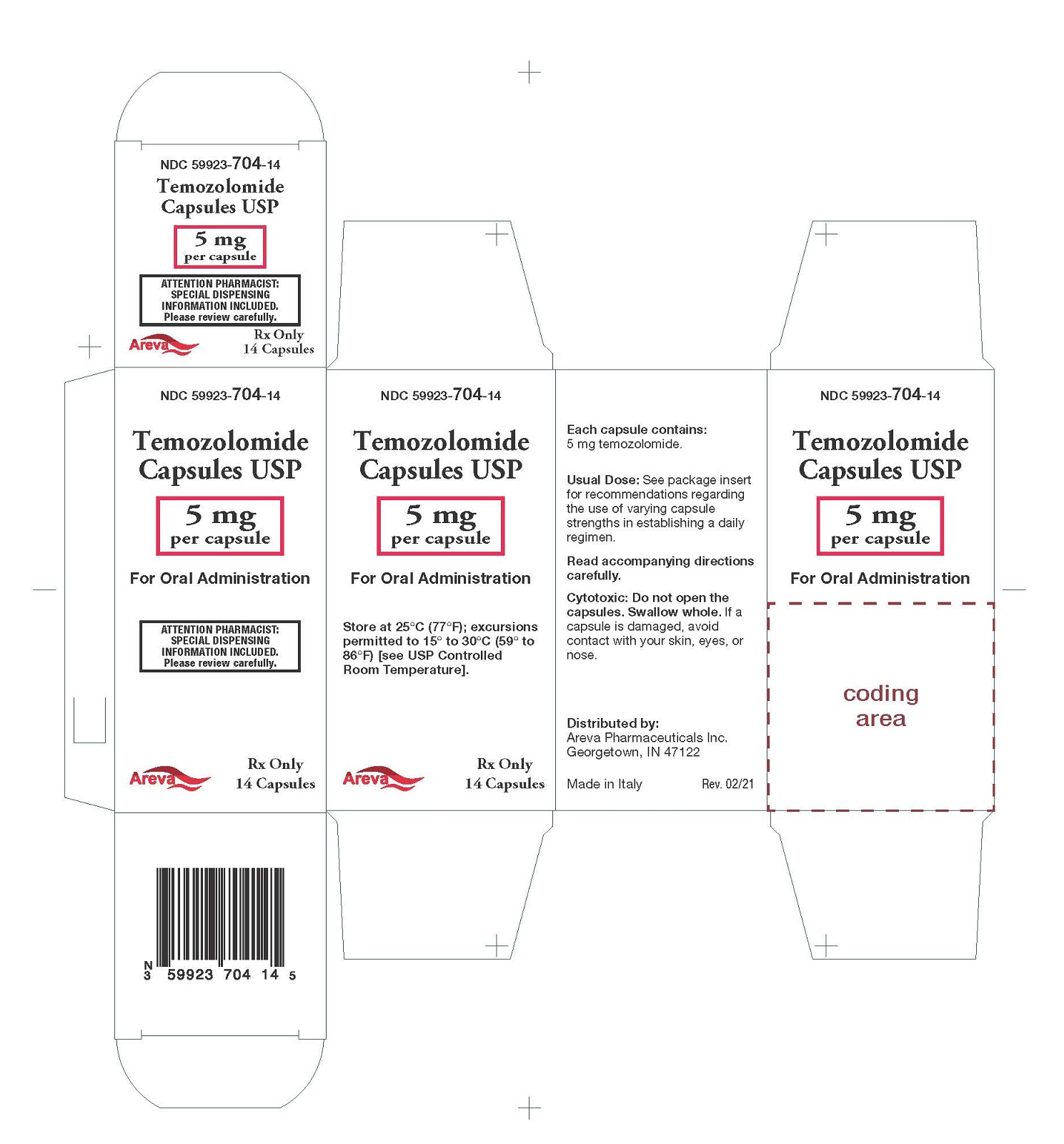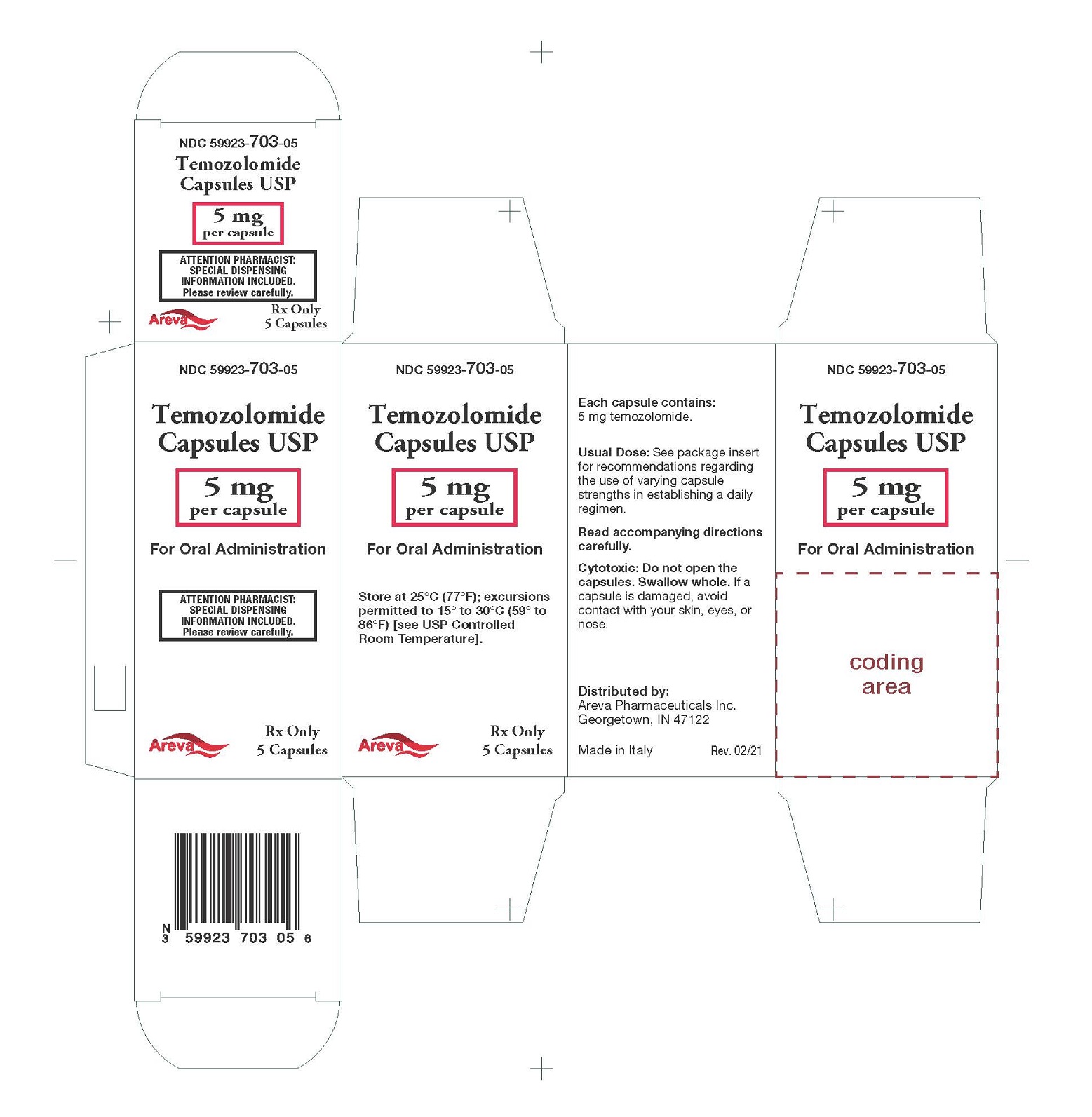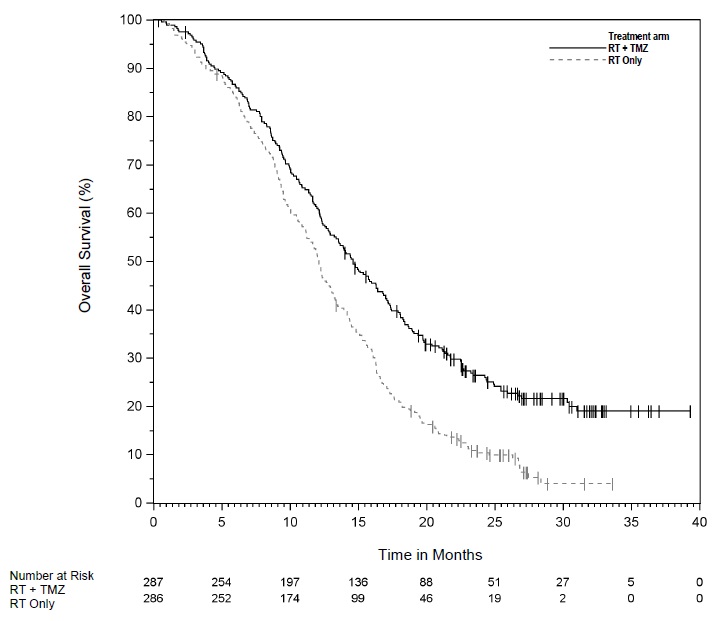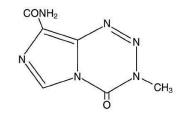 DRUG LABEL: TEMOZOLOMIDE
NDC: 59923-712 | Form: CAPSULE
Manufacturer: Areva Pharmaceuticals
Category: prescription | Type: HUMAN PRESCRIPTION DRUG LABEL
Date: 20240202

ACTIVE INGREDIENTS: TEMOZOLOMIDE 180 mg/1 1
INACTIVE INGREDIENTS: STEARIC ACID; GELATIN; SHELLAC; PROPYLENE GLYCOL; WATER; TITANIUM DIOXIDE; SODIUM STARCH GLYCOLATE TYPE A POTATO; ANHYDROUS LACTOSE; AMMONIA; POTASSIUM HYDROXIDE; TARTARIC ACID; FERRIC OXIDE RED; FERROSOFERRIC OXIDE; SILICON DIOXIDE

HIGHLIGHTS OF PRESCRIBING INFORMATION

These highlights do not include all the information needed to use TEMOZOLOMIDE CAPSULES USP safely and effectively. See full prescribing information for TEMOZOLOMIDE CAPSULES USP.
TEMOZOLOMIDE capsules USP, for oral use
Initial U.S. Approval: 1999

RECENT MAJOR CHANGES

Indications and Usage (1.2) 09/2023
Dosage and Administration (2.1, 2.2, 2.3, 2.4) 09/2023
Contraindications (4) 09/2023
Warnings and Precautions (5.1, 5.2, 5.4, 5.5, 5.6) 09/2023

1 INDICATIONS AND USAGE

Temozolomide Capsules USP is an alkylating drug indicated for the treatment of adults with:

- Newly diagnosed glioblastoma concomitantly with radiotherapy and then as maintenance treatment. (1.1)
- Anaplastic astrocytoma. (1.2)
  - Adjuvant treatment of adults with newly diagnosed anaplastic astrocytoma. (1.2)
  - Treatment of adults with refractory anaplastic astrocytoma. (1.2)

2 DOSAGE AND ADMINISTRATION

- Newly Diagnosed Glioblastoma:
  - 75 mg/m^2once daily for 42 to 49 days concomitant with focal radiotherapy followed by initial maintenance dose of 150 mg/m^2once daily for Days 1 to 5 of each 28-day cycle for 6 cycles. May increase maintenance dose to 200 mg/m^2for cycles 2 – 6 based on toxicity. (2.1)
  - Provide PneumocystisPneumonia (PCP) prophylaxis during concomitant phase and continue in patients who develop lymphopenia until resolution to Grade 1 or less. (2.1)
- Adjuvant Treatment of Newly Diagnosed Anaplastic Astrocytoma:
  Beginning 4 weeks after the end of radiotherapy, administer Temozolomide Capsules USP orally in a single dose on days 1-5 of a 28-day cycle for 12 cycles. The recommended dosage for Cycle 1 is 150 mg/m^2per day and for Cycles 2 to 12 is 200 mg/m^2if patient experienced no or minimal toxicity in Cycle 1. (2.2)
- Refractory Anaplastic Astrocytoma: Initial dose of 150 mg/m^2once daily on Days 1 to 5 of each 28-day cycle. (2.2)

3 DOSAGE FORMS AND STRENGTHS

- Capsules: 5 mg, 20 mg, 100 mg, 140 mg, 180 mg, and 250 mg (3)

4 CONTRAINDICATIONS

- History of serious hypersensitivity to temozolomide or any other ingredients in Temozolomide Capsules USP and dacarbazine. (4)

5 WARNINGS AND PRECAUTIONS

- Myelosuppression: Monitor absolute neutrophil count (ANC) and platelet count prior to each cycle and during treatment. Geriatric patients and women have a higher risk of developing myelosuppression. (5.1, 8.5)
- Hepatotoxicity: Fatal and severe hepatotoxicity have been reported. Perform liver tests at baseline, midway through the first cycle, prior to each subsequent cycle, and approximately 2 to 4 weeks after the last dose of Temozolomide Capsules USP.
- PneumocystisPneumonia (PCP) : Closely monitor all patients, particularly those receiving steroids, for the development of lymphopenia and PCP. (5.3)
- Secondary Malignancies: Myelodysplastic syndrome and secondary malignancies, including myeloid leukemia, have been observed. (5.4)
- Embryo-Fetal Toxicity: Can cause fetal harm. Advise females of reproductive potential of the potential risk to a fetus and to use effective contraception. Advise male patients with pregnant partners or female partners of reproductive potential to use condoms. (5.5, 8.1, 8.3)
- Exposure to Opened Capsules: Temozolomide Capsules USP should not be opened, chewed, or dissolved but should be swallowed whole with a glass of water. (5.6)

6 ADVERSE REACTIONS

- The most common adverse reactions (≥20%) are: alopecia, fatigue, nausea, vomiting, headache, constipation, anorexia, and convulsions. (6.1)
- The most common Grade 3 to 4 hematologic laboratory abnormalities (≥10%) in patients with anaplastic astrocytoma are: decreased lymphocytes, decreased platelets, decreased neutrophils, and decreased leukocytes. (6.1)

To report SUSPECTED ADVERSE REACTIONS, contact Areva at 1-855-853-4760, or FDA at 1-800-FDA-1088 or www.fda.gov/medwatch.

8 USE IN SPECIFIC POPULATIONS

- Lactation: Advise not to breastfeed. (8.2)

FULL PRESCRIBING INFORMATION

1 INDICATIONS AND USAGE

1.1 Newly Diagnosed Glioblastoma

Temozolomide Capsules are indicated for the treatment of adults with newly diagnosed glioblastoma, concomitantly with radiotherapy and then as maintenance treatment.

1.2 Anaplastic Astrocytoma

Temozolomide Capsules are indicated for the:

- adjuvant treatment of adults with newly diagnosed anaplastic astrocytoma;
- treatment of adults with refractory anaplastic astrocytoma.

2 DOSAGE AND ADMINISTRATION

2.1 Monitoring to Inform Dosage and Administration

Prior to dosing, withhold Temozolomide Capsules until patients have an absolute neutrophil count (ANC) of 1.5 x 10^9/L or greater and a platelet count of 100 x 10^9/L or greater.

For concomitant radiotherapy, obtain a complete blood count prior to initiation of treatment and weekly during treatment.

For the 28-day treatment cycles, obtain a complete blood count prior to treatment on Day 1 and on Day 22 of each cycle. Perform complete blood counts weekly until recovery if the ANC falls below 1.5 x 10^9/L and the platelet count falls below 100 x 10^9/L.

For concomitant use with focal radiotherapy, obtain a complete blood count weekly and as clinically indicated.

2.2 Recommended Dosage and Dosage Modifications for Newly Diagnosed Glioblastoma

Administer Temozolomide Capsules orally once daily for 42 to 49 consecutive days during the concomitant use phase with focal radiotherapy, and then once daily on Days 1 to 5 of each 28-day cycle for 6 cycles during the maintenance use phase.

Provide Pneumocystispneumonia (PCP) prophylaxis during the concomitant use phase and continue in patients who develop lymphopenia until resolution to Grade 1 or less [see Warnings and Precautions (5.3)] .

Concomitant Use Phase:

The recommended dosage of Temozolomide Capsules is 75 mg/m^2once daily for 42 to 49 days in combination with focal radiotherapy. Focal radiotherapy includes the tumor bed or resection site with a 2 to 3 cm margin.

Other administration schedules have been used.

Obtain a complete blood count weekly. The recommended dosage modifications during the concomitant use phase are provided in Table 1.

TABLE 1: Dosage Modifications Due to Adverse Reactions During Concomitant Use Phase

Adverse Reaction | Interruption | Discontinuation
Absolute Neutrophil Count | Withhold Temozolomide if ANC is greater than or equal to 0.5 x 10^9/L and less than 1.5 x 10^9/L. Resume Temozolomide at the same dose when ANC is greater than or equal to 1.5 x 10^9/L. | Discontinue Temozolomide if ANC is less than 0.5 x 10^9/L.
Platelet Count | Withhold Temozolomide if platelet count is greater than or equal to 10 x 10^9/L and less than 100 x 10^9/L. Resume Temozolomide at the same dose when platelet count is greater than or equal to 100 x 10^9/L. | Discontinue Temozolomide if platelet count is less than 10 x 10^9/L.
Non-hematological Adverse Reaction (except for alopecia, nausea, vomiting) | Withhold Temozolomide if Grade 2 adverse reaction occurs. Resume Temozolomide at the same dose when resolution to Grade 1 or less. | Discontinue Temozolomide if Grade 3 or 4 adverse reaction occurs.

Single Agent Maintenance Use Phase:

Beginning 4 weeks after concomitant use phase completion, administer Temozolomide Capsules orally once daily on Days 1 to 5 of each 28-day cycle for 6 cycles. The recommended dosage of Temozolomide Capsules in the maintenance use phase is:

- Cycle 1: 150 mg/m^2per day on days 1 to 5.
- Cycles 2 to 6: may increase to 200 mg/m^2per day on days 1 to 5 before starting Cycle 2 if no dosage interruptions or discontinuations are required (Table 1). If the dose is not escalated at the onset of Cycle 2, do notincrease the dose for Cycles 3 to 6.

Obtain a complete blood count on Day 22 and then weekly until the ANC is above 1.5 x 10^9/L and the platelet count is above 100 x 10^9/L. Do not start the next cycle until the ANC and platelet count exceed these levels.

The recommended dosage modifications due to adverse reactions during the maintenance use phase are provided in Table 2.

If Temozolomide Capsules is withheld, reduce the dose for the next cycle by 50 mg/m^2per day. Permanently discontinue Temozolomide Capsules in patients who are unable to tolerate a dose of 100 mg/m^2per day.

TABLE 2: Dosage Modifications Due to Adverse Reactions During Maintenance and Adjuvant Treatment

Adverse Reactions | Interruption and Dose Reduction | Discontinuation
Absolute Neutrophil Count | Withhold Temozolomide if ANC less than 1 x 10^9/L. When ANC is above 1.5 x 10^9/L, resume Temozolomide at reduced dose for the next cycle. | Discontinue Temozolomide if unable to tolerate a dose of 100 mg/m^2per day.
Platelet Count | Withhold Temozolomide if platelet less than 50 x 10^9/L. When platelet count is above 100 x 10^9/L, resume Temozolomide at reduced dose for the next cycle. | Discontinue Temozolomide if unable to tolerate a dose of 100 mg/m^2per day.
Non-hematological Adverse Reaction (except for alopecia, nausea, vomiting) | Withhold Temozolomide if Grade 3 adverse reaction. When resolved to Grade 1 or less, resume Temozolomide at reduced dose for the next cycle. | Discontinue Temozolomide if recurrent Grade 3 adverse reaction occurs after dose reduction, if Grade 4 adverse reaction occurs, or if unable to tolerate a dose of 100 mg/m^2per day.

2.3 Recommended Dosage and Dosage Modifications for Refractory Anaplastic Astrocytoma

Adjuvant Treatment of Newly Diagnosed Anaplastic Astrocytoma

Beginning 4 weeks after the end of radiotherapy, administer Temozolomide Capsules USP orally in a single dose on days 1 to 5 of a 28-day cycle for 12 cycles. The recommended dosage of Temozolomide Capsules is:

- Cycle 1: 150 mg/m^2per day on days 1 to 5.
- Cycles 2 to 12: 200 mg/m^2per day on days 1 to 5 if patient experienced no or minimal toxicity in Cycle 1. If the dose was not escalated at the onset of Cycle 2, do notincrease the dose during Cycles 3 to 6.

The recommended complete blood count testing and dosage modifications due to adverse reactions during adjuvant treatment are provided above and in Table 2 [see Dosage and Administration (2.2)] .

Refractory Anaplastic Astrocytoma

The recommended initial dosage of Temozolomide Capsules is 150 mg/m^2once daily on Days 1 to 5 of each 28-day cycle. Increase the Temozolomide Capsules dose to 200 mg/m^2per day if the following conditions are met at the nadir and on Day 1 of the next cycle:

- ANC is greater than or equal to 1.5 x 10^9/L and
- Platelet count is greater than or equal to 100 x 10^9/L.

Continue Temozolomide Capsules until disease progression or unacceptable toxicity.

Obtain a complete blood count on Day 22 and then weekly until the ANC is above 1.5 x 10^9/L and the platelet count is above 100 x 10^9/L and the platelet count is above 100 x 10^9/L. Do not start the next cycle until the ANC and platelet count exceed these levels.

If the ANC is less than 1 x 10^9/L or the platelet count is less than 50 x 10^9/L during any cycle, reduce the Temozolomide Capsules dose for the next cycle by 50 mg/m^2per day. Permanently discontinue Temozolomide Capsules in patients who are unable to tolerate a dose of 100 mg/m^2per day.

2.4 Preparation and Administration

Temozolomide is a hazardous drug. Follow applicable special handling and disposal procedures^1.

Temozolomide capsules

Take Temozolomide Capsules USP at the same time each day. Administer Temozolomide capsules consistently with respect to food (fasting vs. nonfasting) [see Clinical Pharmacology (12.3)] . To reduce nausea and vomiting, take Temozolomide capsules on an empty stomach or at bedtime and consider antiemetic therapy prior to and following Temozolomide administration.

Swallow Temozolomide capsules whole with water. Advise patients not to open, chew, or dissolve the contents of the capsules [see Warnings and Precautions (5.6)] .

If capsules are accidentally opened or damaged, take precautions to avoid inhalation or contact with the skin or mucous membranes. In case of powder contact, wash the affected area with water immediately.

3 DOSAGE FORMS AND STRENGTHS

• Capsules:

- 5 mg capsules have opaque white bodies with green caps. The capsule body is imprinted with the dosage strength.

- 20 mg capsules have opaque white bodies with yellow caps. The capsule body is imprinted with the dosage strength.

- 100 mg capsules have opaque white bodies with pink caps. The capsule body is imprinted with the dosage strength.

- 140 mg capsules have opaque white bodies with blue caps. The capsule body is imprinted with the dosage strength.

- 180 mg capsules have opaque white bodies with orange caps. The capsule body is imprinted with the dosage strength.

- 250 mg capsules have opaque white bodies with white caps. The capsule body is imprinted with the dosage strength.

4 CONTRAINDICATIONS

Temozolomide is contraindicated in patients with a history of serious hypersensitivity reactions to:

- temozolomide or any other ingredients in Temozolomide capsules and
- dacarbazine, since both temozolomide and dacarbazine are metabolized to the same active metabolite 5-(3-methyltriazen-1-yl)-imidazole-4-carboxamide.

Reactions to Temozolomide have included anaphylaxis [see Adverse Reactions (6.2)].

5 WARNINGS AND PRECAUTIONS

5.1 Myelosuppression

Myelosuppression, including pancytopenia, leukopenia and anemia, some with fatal outcomes, have occurred with Temozolomide [see Adverse Reactions (6.1, 6.2)].

In MK-7365-006, myelosuppression usually occurred during the first few cycles of therapy and was generally not cumulative. The median nadirs occurred at 26 days for platelets (range: 21 to 40 days) and 28 days for neutrophils (range: 1 to 44 days). Approximately 10% of patients required hospitalization, blood transfusion, or discontinuation of therapy due to myelosuppression.

Geriatric patients and women have been shown in clinical trials to have a higher risk of developing myelosuppression.

Obtain a complete blood count and monitor ANC and platelet counts before initiation of treatment and as clinically indicated during treatment. When Temozolomide Capsules is used in combination with radiotherapy, obtain a complete blood count prior to initiation of treatment, weekly during treatment, and as clinically indicated [see Dosage and Administration (2.1, 2.2, 2.3)].

For severe myelosuppression, withhold Temozolomide Capsules and then resume at same or reduced dose, or permanently discontinue, based on occurrence [see Dosage and Administration (2.1, 2.2, 2.3)].

5.2 Hepatotoxicity

Fatal and severe hepatotoxicity have been reported in patients receiving Temozolomide Capsules. Perform liver tests at baseline, midway through the first cycle, prior to each subsequent cycle, and approximately two to four weeks after the last dose of Temozolomide Capsules.

5.3 PneumocystisPneumonia

Pneumocystispneumonia (PCP) can occur in patients receiving Temozolomide. The risk of PCP is increased in patients receiving steroids or with longer treatment regimens of Temozolomide Capsules.

For patients with newly diagnosed glioblastoma, provide PCP prophylaxis for all patients during the concomitant phase. Continue PCP prophylaxis in patients who experience lymphopenia, until resolution to Grade 1 or less [see Dosage and Administration (2.1)].

Monitor all patients receiving Temozolomide Capsules for the development of lymphopenia and PCP.

5.4 Secondary Malignancies

The incidence of secondary malignancies is increased in patients treated with Temozolomide -containing regimens. Cases of myelodysplastic syndrome and secondary malignancies, including myeloid leukemia, have been observed following Temozolomide Capsules administration.

5.5 Embryo-Fetal Toxicity

Based on findings from animal studies and its mechanism of action, Temozolomide can cause fetal harm when administered to a pregnant woman. Adverse developmental outcomes have been reported in both pregnant patients and pregnant partners of male patients. Oral administration of Temozolomide to rats and rabbits during the period of organogenesis resulted in embryolethality and polymalformations at doses less than the maximum human dose based on body surface area.

Advise pregnant women and females of reproductive potential of the potential risk to a fetus. Advise females of reproductive potential to use effective contraception during treatment with Temozolomide and for at least 6 months after the final dose. Because of potential risk of genotoxic effects on sperm, advise male patients with female partners of reproductive potential to use condoms during treatment with Temozolomide and for 3 months after the final dose. Advise male patients not to donate semen during treatment with Temozolomide and for 3 months after the final dose [see Use in Specific Populations (8.1, 8.3)].

5.6 Exposure to Opened Capsules

Advise patients not to open, chew or dissolve the contents of the Temozolomide capsules. Swallow capsules whole with a glass of water. If a capsule becomes damaged, avoid contact of the powder contents with skin or mucous membranes. In case of powder contact, wash affected area with water immediately [see Dosage and Administration (2.4)] . If Temozolomide capsules must be opened or the contents must be dissolved, this should be done by a professional trained in safe handling of hazardous drugs using appropriate equipment and safety procedures.

6 ADVERSE REACTIONS

The following clinically significant adverse reactions are described elsewhere in the labeling:

- Myelosuppression [see Warnings and Precautions (5.1)].
- Hepatotoxicity [see Warnings and Precautions (5.2)].
- PneumocystisPneumonia [see Warnings and Precautions (5.3)].
- Secondary Malignancies [see Warnings and Precautions (5.4)].

6.1 Clinical Trials Experience

Because clinical trials are conducted under widely varying conditions, adverse reaction rates observed in the clinical trials of a drug cannot be directly compared to rates in the clinical trials of another drug and may not reflect the rates observed in practice.

Newly Diagnosed Glioblastoma

The safety of Temozolomide capsules was evaluated in Study MK-7365-051 [see Clinical Studies (14.1)].

Severe or life-threatening reactions occurred in 49% of patients treated with Temozolomide capsules; the most common were fatigue (13%), convulsions (6%), headache (5%), and thrombocytopenia (5%).

The most common adverse reactions (≥20%) in patients treated with Temozolomide were alopecia, fatigue, nausea, anorexia, headache, constipation, and vomiting.

Table 3summarizes the adverse reactions in MK-7365-051.

TABLE 3: Adverse Reactions (≥10%) in Patients with Newly Diagnosed Glioblastoma

Adverse Reactions | Concomitant Use Phase |  |  |  | Maintenance Use Phase
Adverse Reactions | Radiation Therapy and Temozolomide N=288* |  | Radiation Therapy Alone N=285 |  | Temozolomide N=224
Adverse Reactions | All Grades (%) | Grades ≥3 (%) (%) | All Grades (%) | Grades ≥3 (%) | All Grades (%) | Grades ≥3 (%)
Skin and Subcutaneous Tissue
Alopecia | 69 | 0 | 63 | 0 | 55 | 0
Rash | 19 | 1 | 15 | 0 | 13 | 1
General
Fatigue | 54 | 7 | 49 | 5 | 61 | 9
Anorexia | 19 | 1 | 9 | <1 | 27 | 1
Headache | 19 | 2 | 17 | 4 | 23 | 4
Gastrointestinal System
Nausea | 36 | 1 | 16 | <1 | 49 | 1
Vomiting | 20 | <1 | 6 | <1 | 29 | 2
Constipation | 18 | 1 | 6 | 0 | 22 | 0
Diarrhea | 6 | 0 | 3 | 0 | 10 | 1
Central and Peripheral Nervous System
Convulsions | 6 | 3 | 7 | 3 | 11 | 3

*One patient who was randomized to radiation therapy-only arm received radiation therapy and Temozolomide.

NOS = not otherwise specified.

Note:Grade 5 (fatal) adverse reactions are included in the Grade ≥3 column.

Clinically relevant adverse reactions in <10% of patients are presented below:

Central & Peripheral Nervous System:memory impairment, confusion
Eye:vision blurred
Gastrointestinal System:stomatitis, abdominal pain
General:weakness, dizziness
Immune System:allergic reaction
Injury:radiation injury not otherwise specified
Musculoskeletal System:arthralgia
Platelet, Bleeding, & Clotting:thrombocytopenia
Psychiatric:insomnia
Respiratory System:coughing, dyspnea
Special Senses Other:taste perversion
Skin & Subcutaneous Tissue:dry skin, pruritus, erythema

When laboratory abnormalities and adverse reactions were combined, Grade 3 or Grade 4 neutrophil abnormalities including neutropenic reactions were observed in 8% of the patients, and Grade 3 or Grade 4 platelet abnormalities including thrombocytopenic reactions, were observed in 14% of the patients.

Newly Diagnosed Anaplastic Astrocytoma

The safety of Temozolomide for the adjuvant treatment of adults with newly diagnosed anaplastic astrocytoma was derived from published literature [see Clinical Studies (14.2)] . The safety of Temozolomide for the adjuvant treatment of patients with newly diagnosed anaplastic astrocytoma was consistent with the known safety profile of Temozolomide capsules.

Refractory Anaplastic Astrocytoma

The safety of Temozolomide was evaluated in Study MK-7365-006 [see Clinical Studies (14.2)].

The most common adverse reactions (≥20%) were nausea, vomiting, headache, fatigue, constipation, and convulsions.

Tables 4and 5summarize the adverse reactions and hematological laboratory abnormalities in MK-7365-006.

TABLE 4: Adverse Reactions (≥10%) in Patients with Refractory Anaplastic Astrocytoma

Adverse Reactions | Temozolomide N=158
 | All Reactions (%) | Grade 3-4 (%)
Gastrointestinal System
Nausea | 53 | 10
Vomiting | 42 | 6
Constipation | 33 | 1
Diarrhea | 16 | 2
General
Headache | 41 | 6
Fatigue | 34 | 4
Asthenia | 13 | 6
Fever | 13 | 2
Central and Peripheral Nervous System
Convulsions | 23 | 5
Hemiparesis | 18 | 6
Dizziness | 12 | 1
Coordination abnormal | 11 | 1
Amnesia | 10 | 4
Insomnia | 10 | 0
Cardiovascular
Edema peripheral | 11 | 1
Resistance Mechanism
Infection viral | 11 | 0

Clinically relevant adverse reactions in <10% of patients are presented below:

Central and Peripheral Nervous System:paresthesia, somnolence, paresis, urinary incontinence, ataxia, dysphasia, convulsions local, gait abnormal, confusion
Endocrine:adrenal hypercorticism
Gastrointestinal System:abdominal pain, anorexia
General:back pain
Metabolic:weight increase
Musculoskeletal System:myalgia
Psychiatric:anxiety, depression
Reproductive Disorders:breast pain female
Respiratory System:upper respiratory tract infection, pharyngitis, sinusitis, coughing
Skin & Appendages:rash, pruritus
Urinary System:urinary tract infection, micturition increased frequency
Vision:diplopia, vision abnormal*

*This item includes blurred vision; visual deficit; vision changes; and vision troubles.

TABLE 5: Grade 3 to 4 Hematologic Laboratory Abnormalities That Worsened from Baseline in Patients with Refractory Anaplastic Astrocytoma Trial

 | Temozolomide*† (%)
Decreased lymphocytes | 55
Decreased platelets | 19
Decreased neutrophils | 14
Decreased leukocytes | 11
Decreased hemoglobin | 4

* Change from Grade 0 to 2 at baseline to Grade 3 or 4 during treatment
† Dominator range = 142, 158

Hematological Toxicities for Advanced Gliomas

In clinical trial experience with 110 to 111 females and 169 to 174 males (depending on measurements), females experienced higher rates of Grade 4 neutropenia (ANC <0.5 x 10^9/L) and thrombocytopenia (<20 x 10^9/L) than males in the first cycle of therapy (12% vs. 5% and 9% vs. 3%, respectively).

In the entire safety database for which hematologic data exist (N=932), 7% (4/61) and 9.5% (6/63) of patients >70 years experienced Grade 4 neutropenia or thrombocytopenia in the first cycle, respectively. For patients ≤70 years, 7% (62/871) and 5.5% (48/879) experienced Grade 4 neutropenia or thrombocytopenia in the first cycle, respectively. Pancytopenia, leukopenia, and anemia also occurred.

Adverse reactions with Temozolomide for injection

Adverse reactions that were reported in 35 patients who received Temozolomide for injection that were not reported in patients who received Temozolomide capsules were pain, irritation, pruritus, warmth, swelling, and erythema at infusion site; petechiae and hematoma.

6.2 Postmarketing Experience

The following adverse reactions have been identified during post-approval use of Temozolomide capsules. Because these reactions are reported voluntarily from a population of uncertain size, it is not always possible to reliably estimate their frequency or establish a causal relationship to the drug exposure.

Dermatologic: Toxic epidermal necrolysis and Stevens-Johnson syndrome.

Immune System: Hypersensitivity reactions, including anaphylaxis. Erythema multiforme, which resolved after discontinuation of Temozolomide and, in some cases, recurred upon rechallenge.

Hematopoietic: Prolonged pancytopenia, which may result in aplastic anemia and fatal outcomes.

Hepatobiliary: Fatal and severe hepatotoxicity, elevation of liver enzymes, hyperbilirubinemia, cholestasis, and hepatitis.

Infections: Serious opportunistic infections, including some cases with fatal outcomes, can occur with bacterial, viral (primary and reactivated), fungal, and protozoan organisms.

Pulmonary: Interstitial pneumonitis, pneumonitis, alveolitis, and pulmonary fibrosis.

Endocrine: Diabetes insipidus

8 USE IN SPECIFIC POPULATIONS

8.1 Pregnancy

Risk Summary

Based on findings from animal studies and its mechanism of action [see Clinical Pharmacology (12.1)] . Temozolomide can cause fetal harm when administered to a pregnant woman. Available postmarketing reports describe cases of spontaneous abortions and congenital malformations, including polymalformations with central nervous system, facial, cardiac, skeletal, and genitourinary system anomalies with exposure to Temozolomide during pregnancy. These cases report similar adverse developmental outcomes to those observed in animal studies. Administration of Temozolomide to rats and rabbits during the period of organogenesis caused numerous external, internal, and skeletal malformations at doses less than the maximum human dose based on body surface area (see Data) . Advise pregnant women of potential risk to a fetus.

In the U.S. general population, the estimated background risk of major birth defects and miscarriage in clinically recognized pregnancies is 2% to 4% and 15% to 20%, respectively.

Data

Animal Data

Five consecutive days of oral administration of Temozolomide at doses of 75 and 150 mg/m^2(0.38 and 0.75 times the human dose of 200 mg/m^2) in rats and rabbits, respectively, during the period of organogenesis (Gestation Days 8-12) caused numerous malformations of the external and internal organs and skeleton in both species. In rabbits, Temozolomide at the 150 mg/m^2dose (0.75 times the human dose of 200 mg/m^2) caused embryolethality as indicated by increased resorptions.

8.2 Lactation

There are no data on the presence of Temozolomide or its metabolites in human milk, the effects on a breastfed child, or the effects on milk production. Because of the potential for serious adverse reactions, including myelosuppression from Temozolomide in the breastfed children, advise women not to breastfeed during treatment with Temozolomide and for 1 week after the final dose.

8.3 Females and Males of Reproductive Potential

Temozolomide can cause fetal harm when administered to a pregnant woman [see Use in Specific Populations (8.1)].

Pregnancy Testing

Verify pregnancy status in females of reproductive potential prior to initiating Temozolomide [see Use in Specific Population (8.1)].

Contraception

Females

Advise females of reproductive potential to use effective contraception during treatment with Temozolomide and for 6 months after the last dose.

Males

Because of the potential for embryofetal toxicity and genotoxic effects on sperm cells, advise male patients with pregnant partners or female partners of reproductive potential to use condoms during treatment with Temozolomide and for 3 months after the last dose [see Use in Specific Population (8.1), Nonclinical Toxicology (13.1)]. Advise male patients not to donate semen during treatment with Temozolomide and for 3 months after the last dose.

Infertility

Temozolomide may impair male fertility [see Nonclinical Toxicology (13.1)] . Limited data from male patients show changes in sperm parameters during treatment with Temozolomide; however, no information is available on the duration or reversibility of these changes.

8.4 Pediatric Use

Safety and effectiveness of Temozolomide have not been established in pediatric patients. Safety and effectiveness of Temozolomide capsules were assessed, but not established, in 2 open-label studies in pediatric patients aged 3 to 18 years. In one study, 29 patients with recurrent brain stem glioma and 34 patients with recurrent high-grade astrocytoma were enrolled. In a second study conducted by the Children’s Oncology Group (COG), 122 patients were enrolled, including patients with medulloblastoma/PNET (29), high grade astrocytoma (23), low grade astrocytoma (22), brain stem glioma (16), ependymoma (14), other CNS tumors (9), and non-CNS tumors (9). The adverse reaction profile in pediatric patients was similar to adults.

8.5 Geriatric Use

In MK-7365-051, 15% of patients with newly diagnosed glioblastoma were 65 years and older. This study did not include sufficient numbers of patients aged 65 years and older to determine differences in effectiveness from younger patients. No overall differences in safety were observed between patients ≥65 years and younger patients.

The CATNON trial did not include sufficient numbers of patients aged 65 years and older to determine differences in safety or effectiveness when compared to younger patients.

In MK-7365-0006, 4% of patients with refractory anaplastic astrocytoma were 70 years and older. This study did not include sufficient numbers of patients aged 70 years and older to determine differences in effectiveness from younger patients. Patients 70 years and older had a higher incidence of Grade 4 neutropenia (25%) and Grade 4 thrombocytopenia (20%) in the first cycle of therapy than patients less than 70 years of age [see Warnings and Precautions (5.1)and Adverse Reactions (6.1)].

In the entire safety database for which hematologic data exist (N=932), 7% (4/61) and 10% (6/63) of patients >70 years experienced Grade 4 neutropenia or thrombocytopenia in the first cycle, respectively. For patients ≤70 years, 7% (62/871) and 6% (48/879) experienced Grade 4 neutropenia or thrombocytopenia in the first cycle, respectively. Pancytopenia, leukopenia, and anemia also occurred.

8.6 Renal Impairment

No dosage adjustment is recommended for patients with creatinine clearance (CLcr) of 36 to 130 mL/min/m^2 [see Clinical Pharmacology (12.3)]. The recommended dose of Temozolomide has not been established for patients with severe renal impairment (CLcr <36 mL/min/m^2) or for patients with end-stage disease on dialysis.

8.7 Hepatic Impairment

No dosage adjustment is recommended for patients with mild to moderate hepatic impairment (Child Pugh class A and B) [see Clinical Pharmacology (12.3)]. The recommended dose of Temozolomide has not been established for patients with severe hepatic impairment (Child Pugh class C).

10 OVERDOSAGE

Dose-limiting toxicity was myelosuppression and was reported with any dose but is expected to be more severe at higher doses. An overdose of 2000 mg per day for 5 days was taken by one patient and the adverse reactions reported were pancytopenia, pyrexia, multi-organ failure, and death. There are reports of patients who have taken more than 5 days of treatment (up to 64 days), with adverse reactions reported including myelosuppression, which in some cases was severe and prolonged, and infections and resulted in death. In the event of an overdose, monitor complete blood count and provide supportive measures as necessary.

11 DESCRIPTION

Temozolomide is an alkylating drug. The chemical name of temozolomide is 3,4-dihydro-3methyl-4-oxoimidazo[5,1-d]- as-tetrazine-8-carboxamide. The structural formula is:

The material is a white to light tan/light pink powder with a molecular formula of C6H6N6O2and a molecular weight of 194.15. The molecule is stable at acidic pH (< 5) and labile at pH > 7; hence Temozolomide can be administered orally. The prodrug, temozolomide, is rapidly hydrolyzed to the active 5-(3-methyltriazen-1-yl) imidazole-4-carboxamide (MTIC) at neutral and alkaline pH values, with hydrolysis taking place even faster at alkaline pH.

Temozolomide capsules USP:

Temozolomide capsules for oral use contains either 5 mg, 20 mg, 100 mg, 140 mg, 180 mg, or 250 mg of temozolomide.

The inactive ingredients for Temozolomide capsules USP are as follows:

- Temozolomide capsules USP 5 mg: lactose anhydrous (132.8 mg), colloidal silicon dioxide (0.2 mg), sodium starch glycolate (7.5 mg), tartaric acid (1.5 mg), and stearic acid (3 mg).
- Temozolomide capsules USP 20 mg: lactose anhydrous (182.2 mg), colloidal silicon dioxide (0.2 mg), sodium starch glycolate (11 mg), tartaric acid (2.2 mg), and stearic acid (4.4 mg).
- Temozolomide capsules USP 100 mg: lactose anhydrous (175.7 mg), colloidal silicon dioxide (0.3 mg), sodium starch glycolate (15 mg), tartaric acid (3 mg), and stearic acid (6 mg).
- Temozolomide capsules USP 140 mg: lactose anhydrous (246 mg), colloidal silicon dioxide (0.4 mg), sodium starch glycolate (21 mg), tartaric acid (4.2 mg), and stearic acid (8.4 mg).
- Temozolomide capsules USP 180 mg: lactose anhydrous (316.3 mg), colloidal silicon dioxide (0.5 mg), sodium starch glycolate (27 mg), tartaric acid (5.2 mg), and stearic acid (10.8 mg).
- Temozolomide capsules USP 250 mg: lactose anhydrous (154.3 mg), colloidal silicon dioxide (0.7 mg), sodium starch glycolate (22.5 mg), tartaric acid (9 mg), and stearic acid (13.5 mg).

The body of the capsules is made of gelatin, and is opaque white. The cap is also made of gelatin, and the colors vary based on the dosage strength. The capsule body is imprinted with pharmaceutical branding ink, which contains shellac, propylene glycol, strong ammonia solution, potassium hydroxide, and black iron oxide.

- Temozolomide capsules USP 5 mg: The green cap contains gelatin, titanium dioxide, iron oxide yellow and FD&C Blue #2.
- Temozolomide capsules USP 20 mg: The yellow cap contains gelatin, titanium dioxide, and iron oxide yellow.
- Temozolomide capsules USP 100 mg: The pink cap contains gelatin, titanium dioxide and iron oxide red.
- Temozolomide capsules USP 140 mg: The blue cap contains gelatin, titanium dioxide, and FD&C Blue #2.
- Temozolomide capsules USP 180 mg: The orange cap contains gelatin, iron oxide red and titanium dioxide.
- Temozolomide capsules USP 250 mg: The white cap contains gelatin and titanium dioxide.

FDA approved dissolution test specifications differ from USP.

12 CLINICAL PHARMACOLOGY

12.1 Mechanism of Action

Temozolomide is not directly active but undergoes rapid nonenzymatic conversion at physiologic pH to the reactive compound 5-(3-methyltriazen-1-yl)-imidazole-4-carboxamide (MTIC). The cytotoxicity of MTIC is thought to be primarily due to alkylation of DNA, mainly at the O^6and N^7positions of guanine, which causes DNA double strand breaks and results in programmed cell death.

12.2 Pharmacodynamics

Temozolomide exposure-response relationships and the time course of pharmacodynamic response are unknown.

12.3 Pharmacokinetics

Following a single oral dose of 150 mg/m^2, the mean Cmaxis 7.5 mcg/mL for Temozolomide and 282 ng/mL for MTIC.

The mean AUC is 23.4 mcg•hr/mL for Temozolomide and 864 ng•hr/mL for MTIC.

Following a single 90-minute intravenous infusion of 150 mg/m^2, the mean Cmaxvalue for Temozolomide was 7.3 mcg/mL and for MTIC was 276 ng/mL. The mean AUC value for Temozolomide was 24.6 mcg•hr/mL and for MTIC was 891 ng•hr/mL.

Temozolomide exhibits linear kinetics over the therapeutic dosing range of 75 mg/m^2/day to 250 mg/m^2/day.

Absorption

The median Tmaxis 1 hour.

Effect of Food

The mean Cmaxand AUC decreased by 32% and 9%, respectively, and median Tmaxincreased by 2-fold (from 1 to 2.25 hours) when Temozolomide capsules were administered after a modified high-fat breakfast (587 calories comprised of 1 fried egg, 2 strips of bacon, 2 slices of toast, 2 pats of butter, and 8 oz whole milk).

Distribution

Temozolomide has a mean (CV%) apparent volume of distribution of 0.4 L/kg (13%). The mean percent bound of drug-related total radioactivity is 15%.

Elimination

Clearance of temozolomide is about 5.5 L/hr/m^2and the mean elimination half-life is 1.8 hours.

Metabolism

Temozolomide is spontaneously hydrolyzed at physiologic pH to the active species, MTIC and to temozolomide acid metabolite. MTIC is further hydrolyzed to 5-amino-imidazole-4-carboxamide (AIC), which is known to be an intermediate in purine and nucleic acid biosynthesis, and to methylhydrazine, which is believed to be the active alkylating species. Cytochrome P450 enzymes play a minor role in the metabolism of temozolomide and MTIC. Relative to the AUC of temozolomide, the exposure to MTIC and AIC is 2.4% and 23%, respectively.

Excretion

Approximately 38% of the administered temozolomide total radioactive dose is recovered over 7 days: 38% in urine and 0.8% in feces. The majority of the recovered radioactivity in urine is unchanged temozolomide (6%), AIC (12%), temozolomide acid metabolite (2.3%), and unidentified polar metabolite(s) (17%).

Specific Populations

No clinically significant differences in the pharmacokinetics of temozolomide were observed based on age (range: 19 to 78 years), gender, smoking status (smoker vs. non-smoker), creatinine clearance (CLcr) of 36 to 130 mL/min/m^2, or mild to moderate hepatic impairment (Child Pugh class A and B). The pharmacokinetics of temozolomide has not been studies in patients with CLcr < 36 mL/min/m^2, end-stage renal disease on dialysis, or severe hepatic impairment (Child Pugh class C).

Drug Interaction Studies

Clinical Studies and Model-Informed Approaches

No clinically significant differences in the pharmacokinetics of temozolomide or MTIC were observed when co-administered with ranitidine.

No clinically significant differences in the clearance of temozolomide or MTIC were predicted when co-administered with the following drugs: valproic acid, dexamethasone, prochlorperazine, phenytoin, carbamazepine, ondansetron, histamine-2-receptor antagonists, or phenobarbital.

13 NONCLINICAL TOXICOLOGY

13.1 Carcinogenesis, Mutagenesis, Impairment of Fertility

Temozolomide is carcinogenic in rats at doses less than the maximum recommended human dose. Temozolomide induced mammary carcinomas in both males and females at doses 0.13 to 0.63 times the maximum human dose (25-125 mg/m2) when administered orally on 5 consecutive days every 28 days for 6 cycles. Temozolomide also induced fibrosarcomas of the heart, eye, seminal vesicles, salivary glands, abdominal cavity, uterus, and prostate, carcinomas of the seminal vesicles, schwannomas of the heart, optic nerve, and harderian gland, and adenomas of the skin, lung, pituitary, and thyroid at doses 0.5 times the maximum daily dose. Mammary tumors were also induced following 3 cycles of temozolomide at the maximum recommended daily dose.

Temozolomide is a mutagen and a clastogen. In a reverse bacterial mutagenesis assay (Ames assay), temozolomide increased revertant frequency in the absence and presence of metabolic activation. Temozolomide was clastogenic in human lymphocytes in the presence and absence of metabolic activation.

Temozolomide impairs male fertility. Temozolomide caused syncytial cells/immature sperm formation at doses of 50 and 125 mg/m^2(0.25 and 0.63 times the human dose of 200 mg/m^2) in rats and dogs, respectively, and testicular atrophy in dogs at 125 mg/m^2.

13.2 Animal Toxicology and/or Pharmacology

Toxicology studies in rats and dogs identified a low incidence of hemorrhage, degeneration, and necrosis of the retina at temozolomide doses equal to or greater than 125 mg/m^2(0.63 times the human dose of 200 mg/m^2). These changes were most commonly seen at doses where mortality was observed.

14 CLINICAL STUDIES

14.1 Newly Diagnosed Glioblastoma

The efficacy of Temozolomide was evaluated in MK-7365-051 (NCT00006353), a randomized (1:1), multicenter, open-label trial. Eligible patients were required to have newly diagnosed glioblastoma. Patients were randomized to receive either radiation therapy alone or concomitant Temozolomide 75 mg/m^2once daily starting the first day of radiation therapy and continuing the last day of radiation therapy for 42 days (with a maximum of 49 days), followed by Temozolomide 150 mg/m^2or 200 mg/m^2once daily on Days 1 to 5 of each 28-day cycle, starting 4 weeks after the end of radiation therapy and continuing for 6 cycles. In both arms, focal radiation therapy was delivered as 60 Gy/30 fractions and included radiation to the tumor bed or resection site with a 2 to 3-cm margin. PCP prophylaxis was required during the concomitant phase, regardless of lymphocyte count and continued until recovery of lymphocyte count to grade 1 or less. The major efficacy outcome measure was overall survival.

A total of 573 patients were randomized, 287 to Temozolomide and radiation therapy and 286 to radiation therapy alone. At the time of disease progression, Temozolomide was administered as salvage therapy in 161 patients of the 282 (57%) in the radiation therapy alone arm, and 62 patients of the 277 (22%) in the Temozolomide and radiation therapy arm.

The addition of concomitant and maintenance Temozolomide to radiation therapy for the treatment of patients with newly diagnosed glioblastoma showed a statistically significant improvement in overall survival compared to radiotherapy alone (Figure 1). The hazard ratio (HR) for overall survival was 0.63 (95% CI: 0.52, 0.75) with a log-rank P< 0.0001 in favor of the Temozolomide arm. The median overall survival was 14.6 months in the Temozolomide arm and 12.1 months for radiation therapy alone arm.

FIGURE 1: Kaplan-Meier Curves for Overall Survival (ITT Population) in Patients with Newly Diagnosed Glioblastoma in MK-7365-051

14.2 Anaplastic Astrocytoma

Newly Diagnosed Anaplastic Astrocytoma

The efficacy of Temozolomide for the adjuvant treatment of newly diagnosed anaplastic astrocytoma was derived from studies of Temozolomide in the published literature. Temozolomide was evaluated in CATNON (NCT00626990), a randomized, open-label, multicenter trial, where the major efficacy outcome measure was overall survival.

Refractory Anaplastic Astrocytoma

The efficacy of Temozolomide was evaluated in Study MK-7365-006, a single-arm, multicenter trial. Eligible patients had anaplastic astrocytoma at first relapse and a baseline Karnofsky performance status (KPS) of 70 or greater. Patients had previously received radiation therapy and may also have previously received a nitrosourea with or without other chemotherapy. Fifty-four patients had disease progression on prior therapy with both a nitrosourea and procarbazine, and their malignancy was considered refractory to chemotherapy (refractory anaplastic astrocytoma population). Temozolomide capsules were given on Days 1 to 5 of each 28-day cycle at a starting dose of 150 mg/m^2/day. If ANC was ≥1.5 x 10^9/L and platelet count was ≥100 x 10^9/L at the nadir and on Day 1 of the next cycle, the Temozolomide dose was increased to 200 mg/m^2/day. The major efficacy outcome measure was progression-free survival at 6 months and the additional efficacy outcome measures were overall survival and overall response rate.

In the refractory anaplastic astrocytoma population (n=54), the median age was 42 years (range: 19 to 76); 65% were male; and 72% had a KPS of > 80. Sixty-three percent of patients had surgery other than a biopsy at the time of initial diagnosis. Of those patients undergoing resection, 73% underwent a subtotal resection and 27% underwent a gross total resection. Eighteen percent of patients had surgery at the time of first relapse. The median time from initial diagnosis to first relapse was 13.8 months (range: 4.2 months to 6.3 years).

In the refractory anaplastic astrocytoma population, the overall response rate (CR+PR) was 22% (12 of 54 patients) and the complete response rate was 9% (5 of 54 patients). The median duration of all responses was 50 weeks (range: 16 to 114 weeks) and the median duration of complete responses was 64 weeks (range: 52 to 114 weeks). In this population, progression-free survival at 6 months was 45% (95% CI: 31%, 58%) and progression-free survival at 12 months was 29% (95% CI: 16%, 42%). Median progression-free survival was 4.4 months. Overall survival at 6 months was 74% (95% CI: 62%, 86%) and 12-month overall survival was 65% (95% CI: 52%, 78%). Median overall survival was 15.9 months.

15 REFERENCES

1. “OSHA Hazardous Drugs.” OSHA.https://www.osha.gov/hazardous-drugs

16 HOW SUPPLIED/STORAGE AND HANDLING

Temozolomide is a hazardous drug. Follow applicable special handling and disposal procedures.^1

Temozolomide capsules USP

Temozolomide capsules USP are supplied in amber glass bottles with child-resistant caps containing the following capsule strengths:

Temozolomide capsules USP 5 mg: have opaque white bodies with green caps. The capsule body is imprinted with the dosage strength.

They are supplied as follows:

5-count – NDC 59923-703-05

14-count – NDC 59923-704-14

Temozolomide capsules USP 20 mg: have opaque white bodies with yellow caps. The capsule body is imprinted with the dosage strength.

They are supplied as follows:

5-count – NDC 59923-705-05

14-count – NDC 59923-706-14

Temozolomide capsules USP 100 mg: have opaque white bodies with pink caps. The capsule body is imprinted with the dosage strength.

They are supplied as follows:

5-count – NDC 59923-707-05

14-count – NDC 59923-708-14

Temozolomide capsules USP 140 mg: have opaque white bodies with blue caps. The capsule body is imprinted with the dosage strength.

They are supplied as follows:

5-count – NDC 59923-709-05

14-count – NDC 59923-710-14

Temozolomide capsules USP 180 mg: have opaque white bodies with orange caps. The capsule body is imprinted with the dosage strength.

They are supplied as follows:

5-count – NDC 59923-711-05

14-count – NDC 59923-712-14

Temozolomide capsules USP 250 mg: have opaque white bodies with white caps. The capsule body is imprinted with the dosage strength.

They are supplied as follows:

5-count – NDC 59923-713-05

Store Temozolomide capsules USP at 25°C (77°F); excursions permitted to 15° to 30°C (59° to 86°F) [see USP Controlled Room Temperature].

17 PATIENT COUNSELING INFORMATION

Advise the patient to read the FDA-Approved Patient Labeling (Patient Information).

Myelosuppression

Inform patients that Temozolomide can cause low blood cell counts and the need for frequent monitoring of blood cell counts. Advise patients to contact their healthcare provider immediately for bleeding, fever, or other signs of infections [see Warnings and Precautions (5.1)].

Hepatotoxicity

Advise patients of the increased risk of hepatotoxicity and to contact their healthcare provider immediately for signs or symptoms of hepatotoxicity. Inform patients that they will have periodic liver enzyme tests during treatment and following the last dose of Temozolomide [see Warnings and Precautions (5.2)].

PneumocystisPneumonia

Advise patients of the increased risk of Pneumocystis pneumonia and to contact their healthcare provider immediately for new or worsening pulmonary symptoms. Inform patients that prophylaxis for Pneumocystis pneumonia may be needed [see Dosage and Administration (2.1), Warnings and Precautions (5.3)].

Secondary Malignancies

Advise patients of the increased risk of myelodysplastic syndrome and secondary malignancies [see Warnings and Precautions (5.4)].

Exposure to Opened Capsules

Advise patients to not open, chew, or dissolve the capsules. If capsules are accidentally opened or damaged, advise patients to take rigorous precautions with capsule contents to avoid inhalation or contact with the skin or mucous membranes [see Warnings and Precautions (5.6)] . In case of powder contact, wash the affected area with water immediately [see Dosage and Administration (2.4)].

Embryo-Fetal Toxicity

Advise pregnant women and females of reproductive potential of the potential risk to a fetus. Advise females to inform their healthcare provider of a known or suspected pregnancy [see Warnings and Precautions (5.5), Use in Specific Population (8.1)].

Advise females of reproductive potential to use effective contraception during treatment with Temozolomide and for 6 months after the last dose [see Use in Specific Population (8.3)].

Advise male patients with pregnant partners or female partners of reproductive potential to use condoms during treatment with Temozolomide and for 3 months after the last dose [see Use in Specific Population (8.3), Nonclinical Toxicology (13.1)].

Advise male patients not to donate semen during treatment with Temozolomide and for 3 months after the last dose [see Use in Specific Population (8.3), Nonclinical Toxicology (13.1)].

Lactation

Advise women not to breastfeed during treatment with Temozolomide and for 1 week after the final dose [see Use in Specific Population (8.2)].

Infertility

Advise males of reproductive potential that Temozolomide may impair fertility [see Use in Specific Population (8.3), Nonclinical Toxicology (13.1)].

Distributed by:
Areva Pharmaceuticals Inc. Georgetown, IN 47122

Made in Italy

Revised: 05/2023

Patient Information

Temozolomide (TEM-oh-ZOE-loe-mide) capsules USP

What are Temozolomide capsules USP?

Temozolomide capsules are a prescription medicine used to treat adults with certain brain cancer tumors.

It is not known if Temozolomide capsules are safe and effective in children.

Who should not take Temozolomide capsules USP?

Do not take Temozolomide capsules USP if you:

- have had an allergic reaction to temozolomide or any of the other ingredients in Temozolomide capsules. See the end of the leaflet for a list of ingredients in Temozolomide capsules. Symptoms of an allergic reaction with Temozolomide capsules may include: a red itchy rash, or a severe allergic reaction, such as trouble breathing, swelling of the face, throat, or tongue, or severe skin reaction. If you are not sure, ask your healthcare provider.
- have had an allergic reaction to dacarbazine (DTIC), another cancer medicine.

What should I tell my doctor before taking Temozolomide capsules USP?

Tell your healthcare provider about all your medical conditions, including if you:

- have kidney problems
- have liver problems
- are pregnant or plan to become pregnant. Temozolomide capsules can harm your unborn baby and cause birth defects.
  Females who can become pregnant:
  - You should not become pregnant during treatment with Temozolomide capsules.
  - You should use an effective form of birth control (contraception) during treatment and for 6 months after your last dose of Temozolomide capsules.
  - Your healthcare provider should do a pregnancy test to make sure that you are not pregnant before you start taking Temozolomide capsules.
  - Tell your healthcare provider right away if you become pregnant or think you may be pregnant during treatment with Temozolomide capsules.
  Males with a female partner who is pregnant or who can become pregnant:
  - Use a condom for birth control (contraception) during treatment and for 3 months after taking your last dose of Temozolomide capsules.
  - Do notdonate semen during treatment and for 3 months after your last dose of Temozolomide capsules.
- are breast-feeding or plan to breastfeed. It is not known if Temozolomide capsules USP passes into your breast milk. Do not breastfeed during treatment and for 1 week after your last dose of Temozolomide capsules.

Tell your doctor about all the medicines you take, including prescription and non-prescription medicines, vitamins, and herbal supplements.

Know the medicines you take. Keep a list of them and show it to your healthcare provider and pharmacist when you get a new medicine.

How should I take Temozolomide capsules USP?

Temozolomide capsules may be taken by mouth as a capsule.

Take Temozolomide capsules exactly as prescribed by your healthcare provider.

There are 2 common dosing schedules for taking Temozolomide capsules depending on the type of brain cancer tumor that you have.

- People with certain brain cancer tumors take or receive Temozolomide capsules:
  - 1 time each day for 42 to 49 days in a row, along with receiving radiation treatment. This is one cycle of treatment. After this, your healthcare provider may prescribe 6 more cycles of Temozolomide capsules as “maintenance” treatment. For each of these cycles, you take or receive Temozolomide capsules 1 time each day for 5 days in a row and then you stop taking it for the next 23 days. This is a 28-day maintenance treatment cycle.
- People with certain other brain cancer tumors take or receive Temozolomide capsules:
  - 1 time each day for 5 days in a row only, and then you stop taking it for the next 23 days. This is one cycle of treatment (28 days).
  - Your healthcare provider will watch your progress on Temozolomide and decide how long you should take it.
- If your healthcare provider prescribes a treatment regimen that is different from the information in this leaflet, make sure you follow the instructions given to you by your healthcare provider.
- Your healthcare provider may change your dose of Temozolomide capsules, or tell you to stop Temozolomide capsules for a short period of time or permanently if you have certain side effects.
- Your healthcare provider will decide how many treatment cycles of Temozolomide capsules that you will receive, depending on how you respond to and tolerate this treatment.

Temozolomide capsules USP:

- Take Temozolomide capsules exactly as your healthcare provider tells you to.
- Temozolomide capsules contain a white capsule body with a color cap and the colors vary based on the dosage strength. Your healthcare provider may prescribe more than 1 strength of Temozolomide capsules for you, so it is important that you understand how to take your medicine the right way. Be sure that you understand exactly how many capsules you need to take on each day of your treatment, and what strengths to take. This maybe different whenever you start a new cycle.
- Do not take more Temozolomide capsules than prescribed.
- Talk to your healthcare provider or pharmacist before taking your dose if you are not sure how much Temozolomide capsules to take. This will help to prevent taking too much Temozolomide capsules and decrease your chances of getting serious side effects.
- Take each day's dose of Temozolomide capsules at one time, with a full glass of water.
- Take Temozolomide capsules at the same time each day.
- Take Temozolomide capsules the same way each time, either with food or without food.
- Swallow Temozolomide capsules whole. Do notopen, chew, or dissolve the contents of the capsules.
- If Temozolomide capsules are accidentally opened or damaged, be careful not to breathe in (inhale) the powder from the capsules or get the powder on your skin or mucous membranes (for example, in your nose or mouth). If contact with any of these areas happens, wash the area with water right away.
- To help reduce nausea and vomiting, try to take Temozolomide capsules on an empty stomach or at bedtime. Your healthcare provider may prescribe medicine to help prevent or treat nausea, or other medicines to reduce side effects with Temozolomide capsules.
- See your healthcare provider regularly to check your progress. Your healthcare provider will check you for side effects.
- If you take more Temozolomide capsules than prescribed, call your healthcare provider or get emergency medical help right away.

What are the possible side effects of Temozolomide capsules USP?

Temozolomide capsules USP can cause serious side effects, including:

- Decreased blood cell counts.Temozolomide capsules can affect your bone marrow and cause you to have decreased blood cell counts. Decreased white blood cell count, red blood cell count and platelet count are common with Temozolomide capsules but it can also be severe and lead to death.
  - Your healthcare provider will do blood tests regularly to check your blood cell counts before you start and during treatment with Temozolomide capsules.
  - Your healthcare provider may need to change the dose of Temozolomide capsules, or when you get it depending on your blood cell counts.
  - People who are age 70 or older and women have a higher risk for developing decreased blood cell counts during treatment with Temozolomide capsules.
- Secondary cancers.Blood problems such as myelodysplastic syndrome (MDS) and new cancers (secondary cancers), including a certain kind of leukemia, can happen in people who take Temozolomide capsules. Your healthcare provider will monitor you for this.
- Pneumocystispneumonia (PCP).PCP is an infection that people can get when their immune system is weak. Temozolomide capsules decreases white blood cells, which makes your immune system weaker and can increase your risk of getting PCP.
  - People who are taking steroid medicines or who stay on Temozolomide capsules for a longer period of time may have an increased risk of getting PCP infection.
  - Anyone who takes Temozolomide capsules will be watched carefully by their healthcare provider for low blood cell counts and this infection.
  - Tell your healthcare provider if you have any of the following signs and symptoms of PCP infection: shortness of breath, or fever, chills, dry cough.
- Liver problems. Liver problems can happen with Temozolomide capsules and can sometimes be severe and lead to death.Your healthcare provider will do blood tests to check your liver function before you start taking Temozolomide capsules, during treatment, and about 2 to 4 weeks after your last dose of Temozolomide capsules.

Common side effects with Temozolomide capsules include:

- hair loss
- feeling tired
- nausea and vomiting
- headache
- constipation
- loss of appetite
- convulsions

Temozolomide capsules can affect fertility in males and may affect your ability to father a child. Talk with your healthcare provider if fertility is a concern for you.

Tell your healthcare provider about any side effect that bothers you or that does not go away.

These are not all the possible side effects with Temozolomide capsules USP. For more information, ask your healthcare provider or pharmacist.

Call your doctor for medical advice about side effects. You may report side effects to FDA at 1-800-FDA-1088.

How should I store Temozolomide capsules USP?

- Store Temozolomide capsules USP at room temperature between 68°F to 77°F (20°C to 25°C).
- Keep Temozolomide capsules USP out of the reach of children.

General information about the safe and effective use of Temozolomide capsules USP.

Medicines are sometimes prescribed for purposes other than those listed in the Patient Information leaflet. Do not use Temozolomide capsules for a condition for which it was not prescribed. Do not give Temozolomide capsules to other people, even if they have the same symptoms that you have. It may harm them.

You can ask your pharmacist or healthcare provider for information about Temozolomide capsules that is written for health professionals.

For more information, contact Areva at 1-855-853-4760.

What are the ingredients in Temozolomide capsules USP?

Temozolomide capsules USP:

Active ingredient: temozolomide.

Inactive ingredients: lactose anhydrous, colloidal silicon dioxide, sodium starch glycolate, tartaric acid, stearic acid.

The body of the capsules is made of gelatin, and is opaque white. The cap is also made of gelatin, and the colors vary based on the dosage strength. The capsule body is imprinted with pharmaceutical branding ink, which contains shellac, propylene glycol, strong ammonia solution, potassium hydroxide, and black iron oxide.

Temozolomide capsules USP 5 mg: The green cap contains gelatin, titanium dioxide, iron oxide yellow and FD&C Blue #2.

Temozolomide capsules USP 20 mg: The yellow cap contains gelatin, titanium dioxide, and iron oxide yellow.

Temozolomide capsules USP 100 mg: The pink cap contains gelatin, titanium dioxide and iron oxide red.

Temozolomide capsules USP 140 mg: The blue cap contains gelatin, titanium dioxide, and FD&C Blue #2.

Temozolomide capsules USP 180 mg: The orange cap contains gelatin, iron oxide red and titanium dioxide.

Temozolomide capsules USP 250 mg: The white cap contains gelatin and titanium dioxide.

Trademarks are the property of their respective owners.

Distributed by:
Areva Pharmaceuticals Inc. Georgetown, IN 47122

Made in Italy

Revised: 05/2023

PACKAGE LABEL

Principal Display Panel - 5 mg per capsule, 5 capsules

NDC 59923-703-05

Temozolomide Capsules

5 mg per capsule

For Oral Administration

Rx Only 5 Capsules

Principal Display Panel - 5 mg per capsule, 14 capsules

NDC 59923-704-14

Temozolomide Capsules

5 mg per capsule

For Oral Administration

Rx Only 14 Capsules

Principal Display Panel - 20 mg per capsule, 5 capsules

NDC 59923-705-05

Temozolomide Capsules

20 mg per capsule

For Oral Administration

Rx Only 5 Capsules

Principal Display Panel - 20 mg per capsule, 14 capsules

NDC 59923-706-14

Temozolomide Capsules

20 mg per capsule

For Oral Administration

Rx Only 14 Capsules

Principal Display Panel - 100 mg per capsule, 5 capsules

NDC 59923-707-05

Temozolomide Capsules

100 mg per capsule

For Oral Administration

Rx Only 5 Capsules

Principal Display Panel - 100 mg per capsule, 14 capsules

NDC 59923-708-14

Temozolomide Capsules

100 mg per capsule

For Oral Administration

Rx Only 14 Capsules

Principal Display Panel - 140 mg per capsule, 5 capsules

NDC 59923-709-05

Temozolomide Capsules

140 mg per capsule

For Oral Administration

Rx Only 5 Capsules

Principal Display Panel - 140 mg per capsule, 14 capsules

NDC 59923-710-14

Temozolomide Capsules

140 mg per capsule

For Oral Administration

Rx Only 14 Capsules

Principal Display Panel - 180 mg per capsule, 5 capsules

NDC 59923-711-05

Temozolomide Capsules

180 mg per capsule

For Oral Administration

Rx Only 5 Capsules

Principal Display Panel - 180 mg per capsule, 14 capsules

NDC 59923-712-14

Temozolomide Capsules

180 mg per capsule

For Oral Administration

Rx Only 14 Capsules

Principal Display Panel - 250 mg per capsule, 5 capsules

NDC 59923-713-05

Temozolomide Capsules

250 mg per capsule

For Oral Administration

Rx Only 5 Capsules